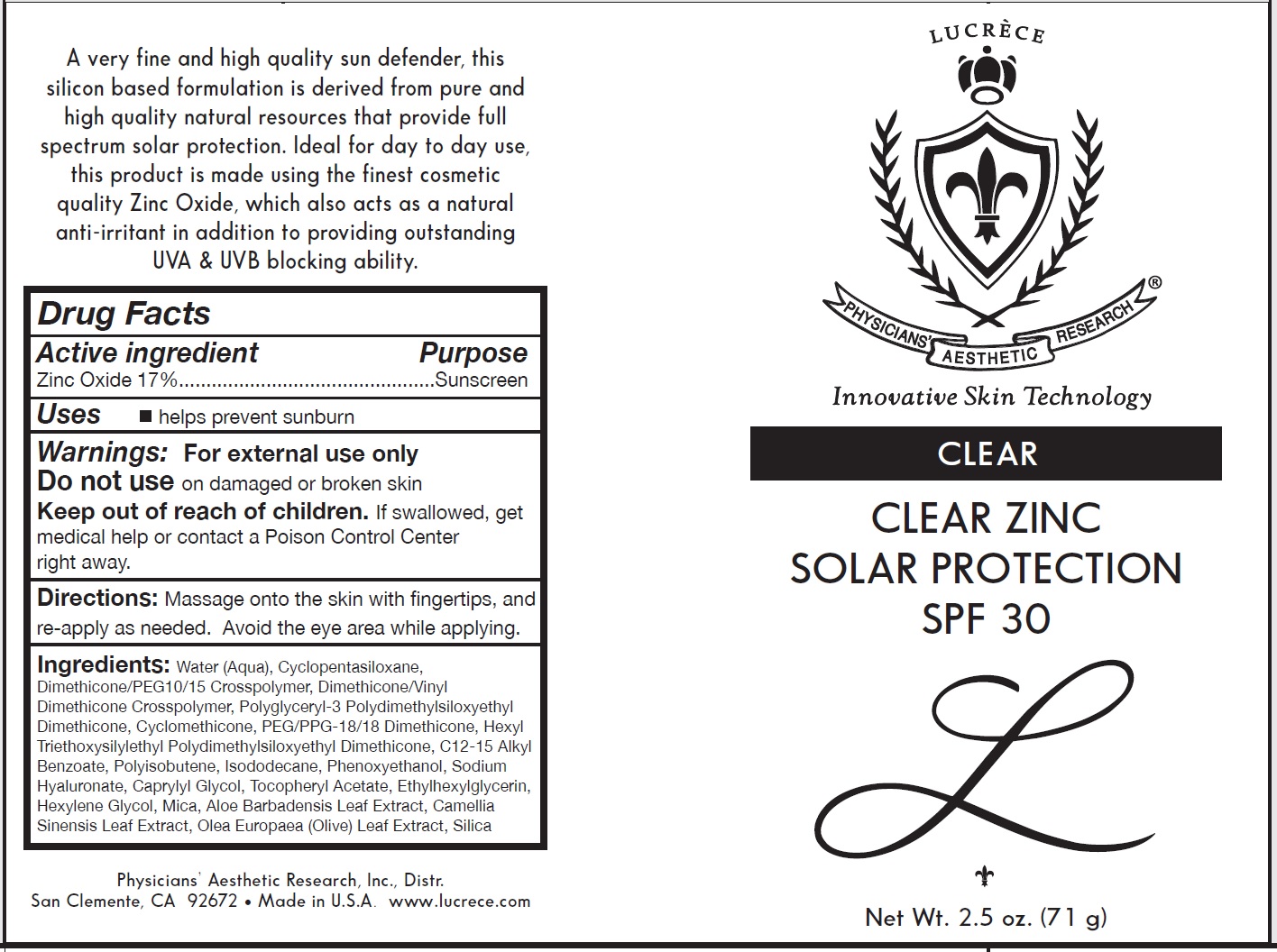 DRUG LABEL: Clear Clear Zinc Solar Protection SPF 30
NDC: 62742-4109 | Form: CREAM
Manufacturer: Allure Labs, LLC
Category: otc | Type: HUMAN OTC DRUG LABEL
Date: 20241205

ACTIVE INGREDIENTS: ZINC OXIDE 170 mg/1 g
INACTIVE INGREDIENTS: WATER; CYCLOMETHICONE 5; DIMETHICONE/VINYL DIMETHICONE CROSSPOLYMER (SOFT PARTICLE); POLYGLYCERYL-3 POLYDIMETHYLSILOXYETHYL DIMETHICONE (4000 MPA.S); CYCLOMETHICONE; PEG/PPG-18/18 DIMETHICONE; ALKYL (C12-15) BENZOATE; POLYISOBUTYLENE (1000 MW); ISODODECANE; PHENOXYETHANOL; HYALURONATE SODIUM; CAPRYLYL GLYCOL; .ALPHA.-TOCOPHEROL ACETATE; ETHYLHEXYLGLYCERIN; HEXYLENE GLYCOL; MICA; ALOE VERA LEAF; CAMELLIA SINENSIS FLOWER; OLEA EUROPAEA LEAF; SILICON DIOXIDE

Drug Facts

ACTIVE INGREDIENT

Zinc Oxide: 17%

Purpose:

Suncreen

INDICATIONS AND USAGE

Uses: Help prevent sunburn

Warnings: For external use only

Do not use on damged or broken skin.

Keep out of reach of children. if swalloed, get medical help or contact a Poison Control Center right away.

DOSAGE AND ADMINISTRATION

Directions: Massage into skin with fingertips and reapply as needed. Avoid eye area while applying.

INACTIVE INGREDIENT

Other Ingredients: Water (Aqua), Cyclopentasiloxane, Dimethicone/PEG10/15 Crosspolymer, Dimethicone/Vinyl Dimethicone Crossploymer, Polyglyceryl-3 polydimethylsiloxyethyl Dimethicone, Cyclomethicone, PEG/PPG-18/18 Dimethicone, Hexyl Triethoxysilylethyl Polydimethylsiloxyethyl Dimethicone, C12-15 Alkyl Benzoate, Polyisobutene, Isododecane, Phenoxyethanol, Sodium Hyaluronate, Caprylyl Glycol, Tocopheryl Acetate, Ethylhexylglycerin, Hexylene Glycol, Mica, Aloe Barbadensis Leaf extract, Camellia Sinensis Leaf Extract, Olea Europaea (Olive) Leaf Extract, Silica

PACKAGE LABEL

Physicians' Aesthetic Research, Inc. Distr.

San Clemente, CA 92672 . Made in U.S.A. www.lucrece.com